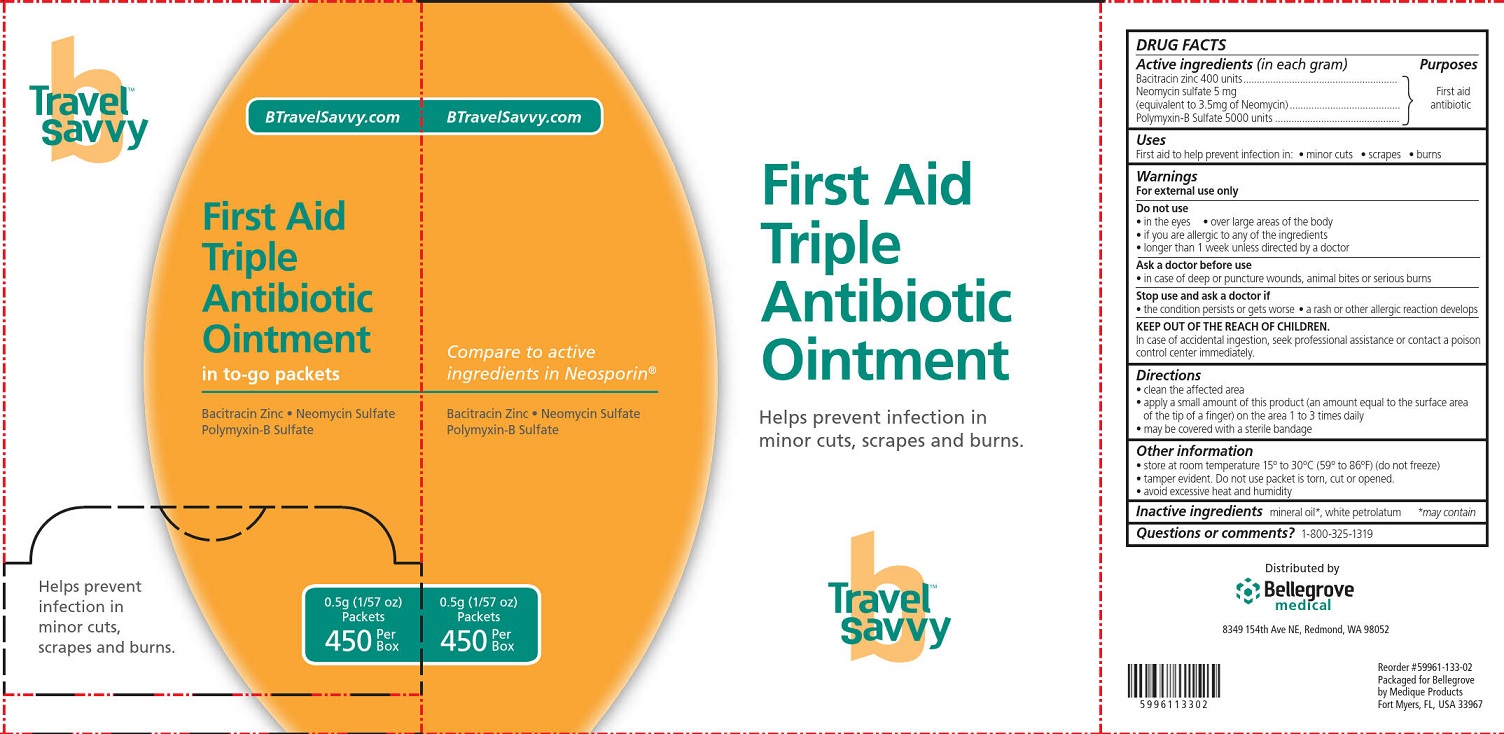 DRUG LABEL: Travel Savvy First Aid Triple Antibiotic
NDC: 59961-143 | Form: OINTMENT
Manufacturer: Bellegrove Medical Supply, Inc.
Category: otc | Type: HUMAN OTC DRUG LABEL
Date: 20240116

ACTIVE INGREDIENTS: BACITRACIN ZINC 400 [USP'U]/1 g; NEOMYCIN SULFATE 3.5 mg/1 g; POLYMYXIN B SULFATE 5000 [USP'U]/1 g
INACTIVE INGREDIENTS: PETROLATUM

First Aid Triple Antibiotic Ointment

Active ingredients

Bacitracin Zinc 400 units

Neomycin sulfate 5 mg
(equivalent to 3.5 mg of Neomycin)

Polymyxin B Sulfate 5000 units

Purpose

First aid antibiotic

Uses

First aid to help prevent infection in:

- minor cuts
- scrapes
- burns

Warnings

For external use only.

Do not use

- in the eyes
- over large areas of the body
- if you are allergic to any of the ingredients
- longer than 1 week unless directed by a doctor

Ask a doctor before use

- in case of deep puncture wounds, animal bites or serious burns

Stop use and ask a doctor if

- the condition persists or gets worse
- a rash or other allergic reaction develops

Keep out of reach of children.

In case of accidental ingestion, seek professional assistance or contact a poison control center immediately.

Directions

- clean the affected area
- apply a small amount of this product (an amount equal to the surface area of the tip of a finger) on the area 1 to 3 times daily
- may be covered with a sterile bandage

Other information

- store at room temperature 15° to 25°C (59° to 77°F) (do not freeze)
- do not use any open or torn packets
- avoid excessive heat and humidity

Inactive ingredients

mineral oil*, white petrolatum

* May contain

Questions or comments?

1-800-325-1319

Travel Savvy First Aid Triple Antibiotic Ointment Label

Travel Savvy™

BTravelSavvy.com

First Aid Triple Antibiotic Ointment

in to-go packets

Bacitracin Zinc • Neomycin Sulfate

Polymyxin-B Sulfate

Helps prevent infection in minor cuts, scrapes and burns.

0.5g (1/57 oz)

Packets

450 Per Box